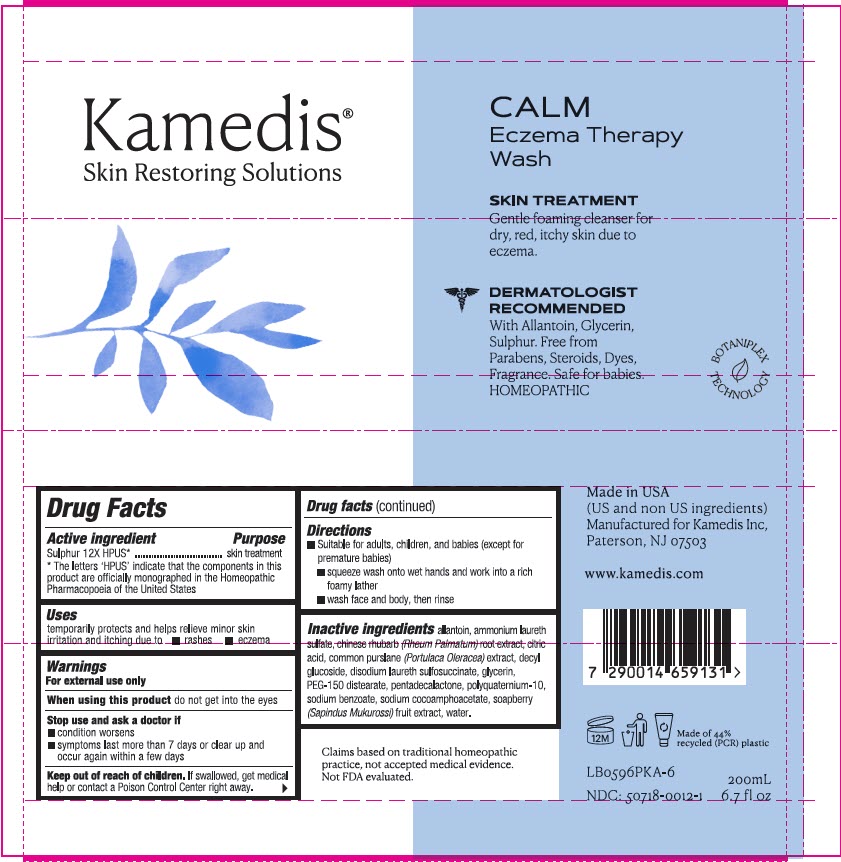 DRUG LABEL: Calm Eczema Therapy Wash
NDC: 50718-0012 | Form: LIQUID
Manufacturer: Kamedis
Category: homeopathic | Type: HUMAN OTC DRUG LABEL
Date: 20240130

ACTIVE INGREDIENTS: SULFUR 12 [hp_X]/1 mL
INACTIVE INGREDIENTS: ALLANTOIN; CITRIC ACID MONOHYDRATE; DECYL GLUCOSIDE; DISODIUM LAURETH SULFOSUCCINATE; GLYCERIN; PEG-150 DISTEARATE; PENTADECALACTONE; SODIUM BENZOATE; SODIUM COCOAMPHOACETATE; WATER; RHEUM PALMATUM ROOT; SAPINDUS MUKOROSSI FRUIT; PURSLANE; AMMONIUM LAURETH-2 SULFATE; POLYQUATERNIUM-10 (10000 MPA.S AT 2%)

Calm Eczema Therapy Wash

Drug Facts

Active ingredient

Sulphur 12X HPUS*
* The letters 'HPUS' indicate that the components in this product are officially monographed in the Homeopathic Pharmacopoeia of the United States

Purpose

Skin Treatment

Use

- temporarily protects and helps relieve minor skin irritation and itching due to:
- rashes
- eczema

Warnings

For external use only

When using this product

- do not get into eyes

Stop use and ask a doctor if

- condition worsens
- symptoms last more than 7 days or clear up and occur again within a few days

Keep out of reach of children.

- If swallowed, get medical help or contact a Poison Control Center right away.

Directions

- Suitable for adults, children, and babies (except for premature babies)
  - squeeze wash onto wet hands and work into a rich foamy lather
  - wash face and body, then rinse

Inactive Ingredients

allantoin, ammonium laureth sulfate, Chinese rhubarb (Rheum palmatum) root extract, citric acid, common purslane (Portulaca oleracea) extract, decyl glucoside, disodium laureth sulfosuccinate, glycerin, PEG-150 distearate, pentadecalactone, polyquaternium-10, sodium benzoate, sodium cocoamphoacetate, soapberry (Sapindus mukurossi) fruit extract, water

Claims based on traditional homeopathic practice, not accepted medical evidence. Not FDA evaluated.

Made in USA
(US and non-US ingredients)
Manufactured for Kamedis
Paterson, NJ 07503
1-855-626-6606

www.KamedisUSA.com

PRINCIPAL DISPLAY PANEL - 200 mL Tube Label

Kamedis®
Skin Restoring Solutions

CALM
Eczema Therapy
Wash

SKIN TREATMENT
Gentle foaming cleanser for
dry, red, itchy skin due to
eczema.

DERMATOLOGIST
RECOMMENDED
With Allantoin, Glycerin,
Sulphur. Free from
Parabens, Steroids, Dyes,
Fragrance. Safe for babies.
HOMEOPATHIC

BOTANIPLEX
TECHNOLOGY